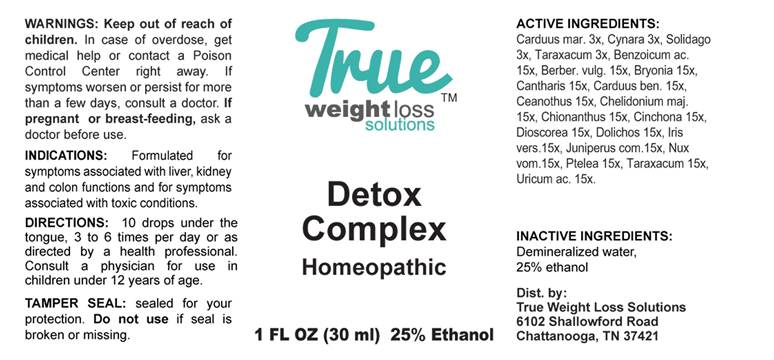 DRUG LABEL: Detox Complex
NDC: 73162-0002 | Form: LIQUID
Manufacturer: Health Masters LLC
Category: homeopathic | Type: HUMAN OTC DRUG LABEL
Date: 20240122

ACTIVE INGREDIENTS: MILK THISTLE 3 [hp_X]/1 mL; CYNARA SCOLYMUS LEAF 3 [hp_X]/1 mL; SOLIDAGO VIRGAUREA FLOWERING TOP 3 [hp_X]/1 mL; TARAXACUM OFFICINALE 3 [hp_X]/1 mL; BENZOIC ACID 15 [hp_X]/1 mL; BERBERIS VULGARIS ROOT BARK 15 [hp_X]/1 mL; BRYONIA ALBA ROOT 15 [hp_X]/1 mL; LYTTA VESICATORIA 15 [hp_X]/1 mL; CENTAUREA BENEDICTA 15 [hp_X]/1 mL; CEANOTHUS AMERICANUS LEAF 15 [hp_X]/1 mL; CHELIDONIUM MAJUS WHOLE 15 [hp_X]/1 mL; CHIONANTHUS VIRGINICUS BARK 15 [hp_X]/1 mL; CINCHONA OFFICINALIS BARK 15 [hp_X]/1 mL; DIOSCOREA VILLOSA TUBER 15 [hp_X]/1 mL; MUCUNA PRURIENS FRUIT TRICHOME 15 [hp_X]/1 mL; IRIS VERSICOLOR ROOT 15 [hp_X]/1 mL; JUNIPER BERRY 15 [hp_X]/1 mL; STRYCHNOS NUX-VOMICA SEED 15 [hp_X]/1 mL; PTELEA TRIFOLIATA BARK 15 [hp_X]/1 mL; URIC ACID 15 [hp_X]/1 mL
INACTIVE INGREDIENTS: WATER; ALCOHOL

Drug Facts:

ACTIVE INGREDIENTS:

Carduus Marianus 3x, Cynara Scolymus 3x, Solidago Virgaurea 3x, Taraxacum Officinale 3x, Benzoicum Acidum 15x, Berberis Vulgaris 15x, Bryonia (Alba) 15x, Cantharis 15x, Carduus Benedictus 15x, Ceanothus Americanus 15x, Chelidonium Majus 15X, Chionanthus Virginica 15X, Cinchona Officinalis 15X, Dioscorea Villosa 15x, Dolichos Pruriens 15x, Iris Versicolor 15x, Juniperus Communis 15x, Nux Vomica 15x, Ptelea Trifoliata 15x, Taraxacum Officinale 15x, Uricum Acidum 15x.

INDICATIONS:

Formulated for symptoms associated with liver, kidney and colon functions and for symptoms associated with toxic conditions.

WARNINGS:

Keep out of reach of children. In case of overdose, get medical help or contact a Poison Control Center right away.

If symptoms worsen or persist for more than a few days, consult a doctor.

If pregnant or breast-feeding, ask a doctor before use.

TAMPER SEAL: sealed for your protection. Do not use if seal is broken or missing.

Keep out of reach of children. In case of overdose, get medical help or contact a Poison Control Center right away.

DIRECTIONS:

10 drops under the tongue, 3 to 6 times per day or as directed by a health professional. Consult a physician for use in children under 12 years of age.

INDICATIONS:

Formulated for symptoms associated with liver, kidney and colon functions and for symptoms associated with toxic conditions.

INACTIVE INGREDIENTS:

Demineralized water, 25% ethanol.

QUESTIONS:

Dist. by:

Health Masters LLC

3386 CR 427

Waterloo, IN 46793

PACKAGE LABEL DISPLAY:

TRUE
weight loss
solutions

Detox

Complex

Homeopathic

1 FL OZ (30 ml)